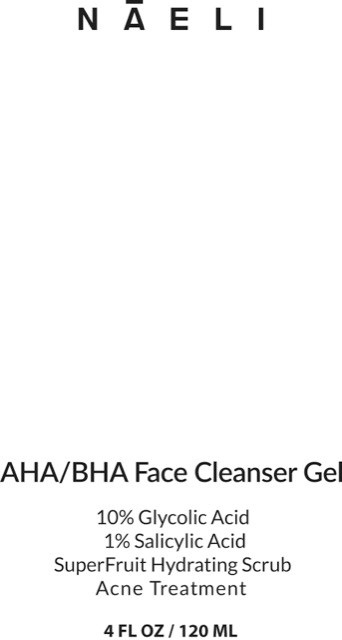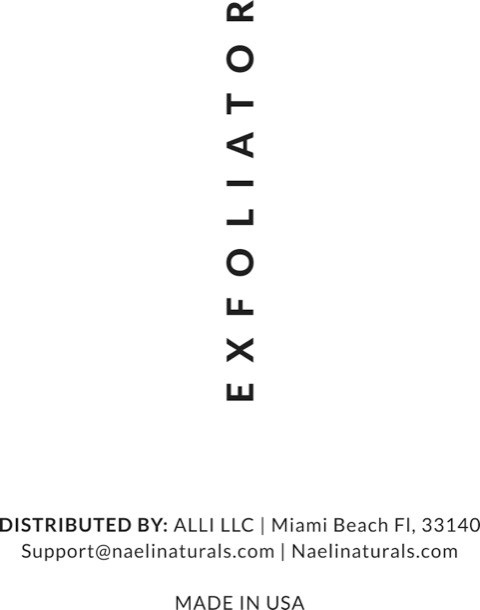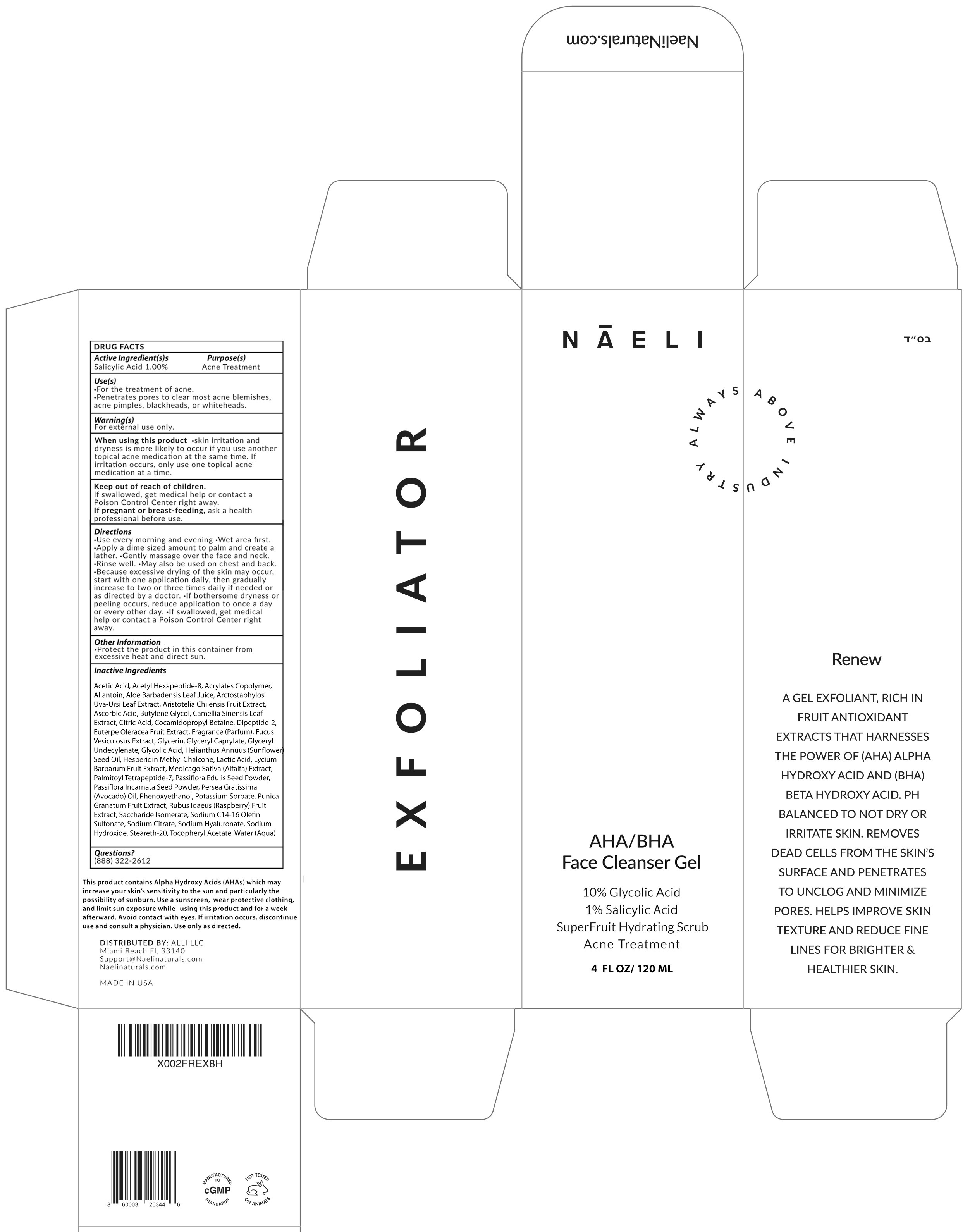 DRUG LABEL: NAELI Exfoliator AHA BHA Face Cleanser
NDC: 73670-620 | Form: GEL
Manufacturer: ALLI LLC
Category: otc | Type: HUMAN OTC DRUG LABEL
Date: 20250623

ACTIVE INGREDIENTS: SALICYLIC ACID 10 mg/1 mL
INACTIVE INGREDIENTS: ACETIC ACID; ACETYL HEXAPEPTIDE-8 AMIDE; ALLANTOIN; ALOE VERA LEAF JUICE; ARCTOSTAPHYLOS UVA-URSI LEAF; ARISTOTELIA CHILENSIS FRUIT; ASCORBIC ACID; BUTYLENE GLYCOL; GREEN TEA LEAF; CITRIC ACID MONOHYDRATE; COCAMIDOPROPYL BETAINE; DIPEPTIDE-2; ACAI; FUCUS VESICULOSUS; GLYCERIN; GLYCERYL MONOCAPRYLATE; GLYCOLIC ACID; SUNFLOWER OIL; HESPERIDIN METHYL CHALCONE; LACTIC ACID; LYCIUM BARBARUM FRUIT; MEDICAGO SATIVA WHOLE; PALMITOYL TETRAPEPTIDE-7; PASSIFLORA EDULIS SEED; PASSIFLORA INCARNATA SEED; AVOCADO OIL; PHENOXYETHANOL; POTASSIUM SORBATE; POMEGRANATE; RASPBERRY; SACCHARIDE ISOMERATE; SODIUM C14-16 OLEFIN SULFONATE; SODIUM CITRATE; SODIUM HYALURONATE; SODIUM HYDROXIDE; STEARETH-20; .ALPHA.-TOCOPHEROL ACETATE; WATER

NAELI Exfoliator AHA BHA Face Cleanser Gel

Active Ingredient(s)s

Salicylic Acid 1.00%

Purpose(s)

Acne Treatment

Use(s)

- For the treatment of acne.
- Penetrates pores to clear most acne blemishes, acne pimples, blackheads, or whiteheads.

Warning(s)

For external use only.

When using this product

- skin irritation and dryness is more likely to occur if you use another topical acne medication at the same time. If irritation occurs, only use one topical acne medication at a time.

Keep out of reach of children.

If swallowed, get medical help or contact a Poison Control Center right away.

If pregnent or breast-feeding,

ask a health professional before use.

Directions

- Use every morning and evening
- Wet area first.
- Apply a dime sized amount to palm and create a lather.
- Gently massage over the face and neck.
- Rinse well.
- May also be used on chest and back.
- Because excessive drying of the skin may occur, start with one application daily, then gradually increase to two or three times daily if needed or as directed by a doctor.
- If bothersome dryness or peeling occurs, reduce application to once a day or every other day.
- If swallowed, get medical help or contact a Poison Control Center right away.

Other Information

- Protect the product in this container from excessive heat and direct sun.

Inactive Ingredients

Acetic Acid, Acetyl Hexapeptide-8, Acrylates Copolymer, Allantoin, Aloe Barbadensis leaf Juice, Acrtostaphylos Uva-Ursi Leaf Extract, Aristotelia Chilensis Fruit Extract, Ascorbic Acid, Butylene Glycol, Camellia Sinensis Leaf Extract, Citric Acid, Cocamidopropyl Betaine, Dipeptide-2, Euterpe Oleracea Fruit Extract, Fragrance (Parfum), Fucus Vesiculosus Extract, Glycerin, Glyceryl Caprylate, Glyceryl Undecylenate, Glycolic Acid, Helianthus Annuus (Sunflower) Seed Oil, Hesperidin Methyl Chalcone, Lactic Acid, Lycium Barbarum Fruit Extract, Medicago Sativa (Alfalfa) Extract, Palmitoyl Tetrapeptide-7, Passiflora Edulis Seed Powder, Passiflora Incarnata Seed Powder, Persea Gratissima (Avocado) Oil, Phenoxyethanol, Potassium Sorbate, Punica Granatum Fruit Extract, Rubus Idaeus (Raspberry) Fruit Extract, Saccharide Isomerate, Sodium C14-16 Olefin Sulfonate, Sodium Citrate, Sodium Hyaluronate, Sodium Hydroxide, Steareth-20, Tocopheryl Acetate, Water (Aqua)

Questions?

(888) 322-2612